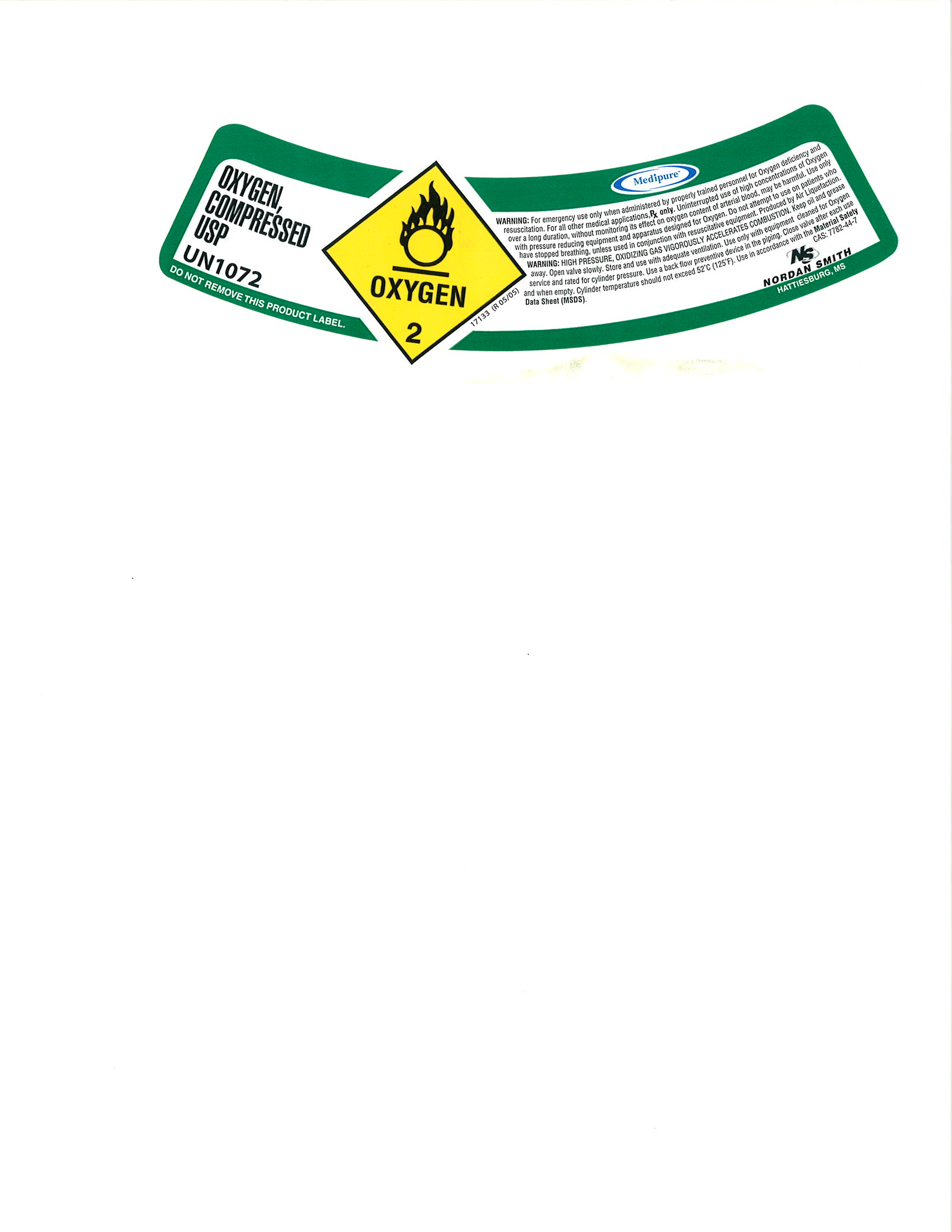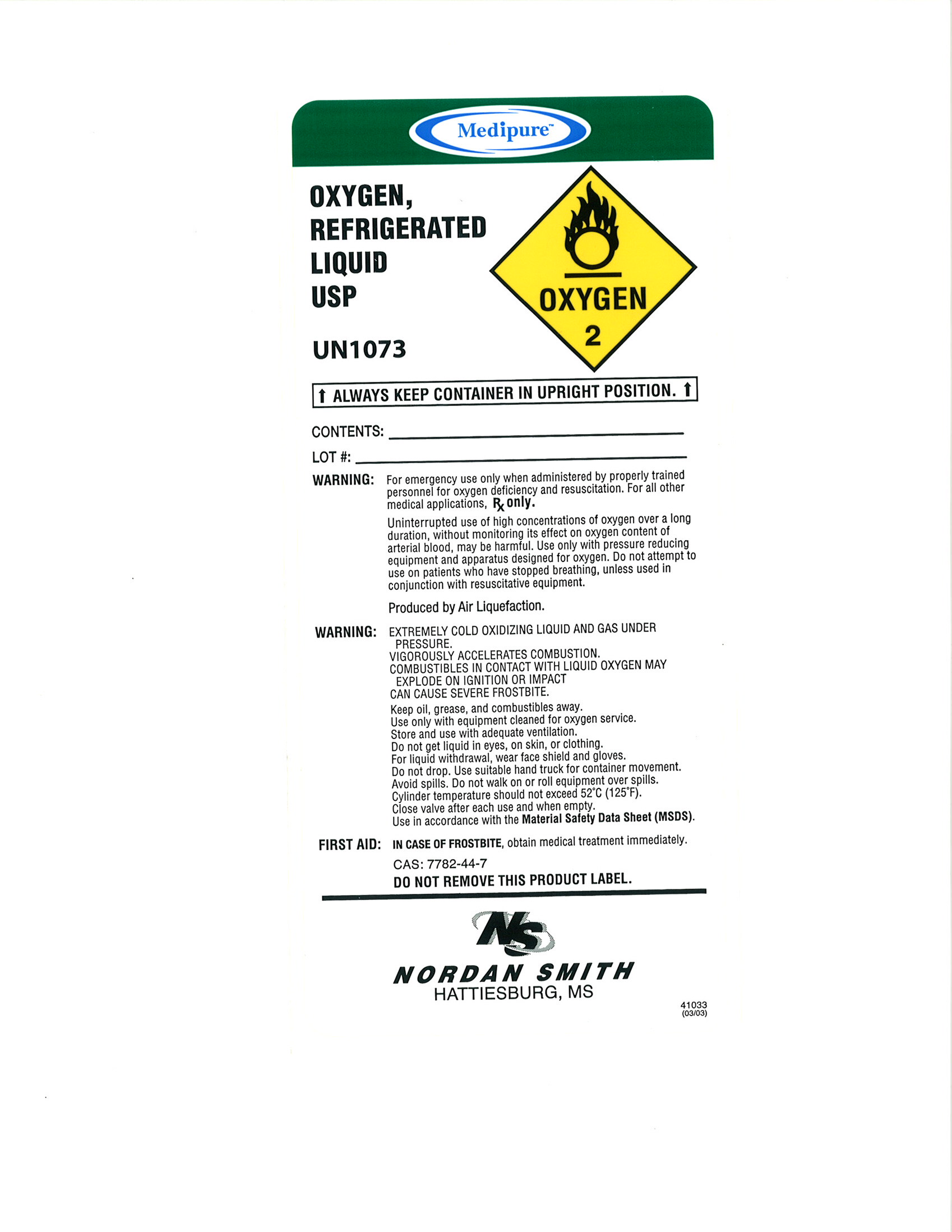 DRUG LABEL: Oxygen
NDC: 54416-001 | Form: GAS
Manufacturer: Nordan Smith Welding Supply
Category: prescription | Type: HUMAN PRESCRIPTION DRUG LABEL
Date: 20091217

ACTIVE INGREDIENTS: Oxygen 995 mL/1 L

Oxygen Label

PACKAGE LABEL

OXYGEN, COMPRESSED USP
UN1072
DO NOT REMOVE THIS PRODUCT LABEL.
OXYGEN 2
Medipure
WARNING: For emergency use only when administered by properly trained personnel for Oxygen deficiency and resuscitation. For all other medical applications, RX only. Uninterrupted use of high concentrations of Oxygen over a long duration, without monitoring its effect on oxygen content of arterial blood, may be harmful. Use only with pressure reducing equipment and apparatus designed for Oxygen. Do not attempt to use on patients who have stopped breathing , unless used in conjunction with resuscitative equipment. Produced by Air Liquefaction. WARNING: HIGH PRESSURE, OXIDIZING GAS VIGORUSLEY ACCELERATES COMBUSTION. Keep oil and grease away. Open valve slowly. Store and use with adequate ventilation. Use only with equipment cleaned for Oxygen service and rated for cylinder pressure. Use a back flow preventive device in the piping. Close valve after each use and when empty. Cylinder temperature should not exceed 52°C (125°F). Use in accordance with the Material Safety Data Sheet (MSDS).
CAS: 7782-44-7
N/S NORDAN SMITH HATTIESBURG, MS.
17133 (R 05/05)

Oxygen Refrigerated Liquid Label

Medipure
OXYGEN, REFRIGERATED LIQUID USP
UN1073
OXYGEN 2
ALWAYS KEEP CONTAINER IN UPRIGHT POSITION.
CONTENTS:_________________________
LOT#:______________________________
WARNING: For emergency use only when administered by properly trained personnel for oxygen deficiency and resuscitation. For all other medical applications. RX only.
Uninterrupted use of high concentrations of oxygen over a long duration, without monitoring its effect on oxygen content of arterial blood, may be harmful. Use only with pressure reducing equipment and apparatus designed for oxygen. Do not attempt to use on patients who have stopped breathing, unless used in conjunction with resuscitative equipment.
Produced by Air Liquefaction.
WARNING: EXTREMELY COLD OXIDIZING LIQUID AND GAS UNDER PRESSURE. VIGOROUSLY ACCELERATES COMBUSTION. COMBUSTIBLES IN CONTACT WITH LIQUID OXYGEN MAY EXPLORE ON IGNITION OR IMPACT CAN CAUSE SEVERE FROSTBITE.
Keep oil, grease, and combustibles away. Use only with equipment cleaned for oxygen service. Store and use with adequate ventilation. Do not get liquid in eyes, on skin, or clothing. For liquid withdrawal, wear face shield and gloves. Do not drop. Use suitable hand truck for container movement. Avoid spills. Do not walk on or roll equipment over spills. Cylinder temperature should not exceed 52°C (125°F). Close valve after each use and when empty. Use in accordance with the Material Safety Data Sheet (MSDS).
FIRST AID: IN CASE OF FROSTBITE, obtain medical treatment immediately.
CAS: 7782-44-7
DO NOT REMOVE THIS PRODUCT LABEL.
N/S NORDAN SMITH HATTIESBURG, MS.
41033 (03/03)